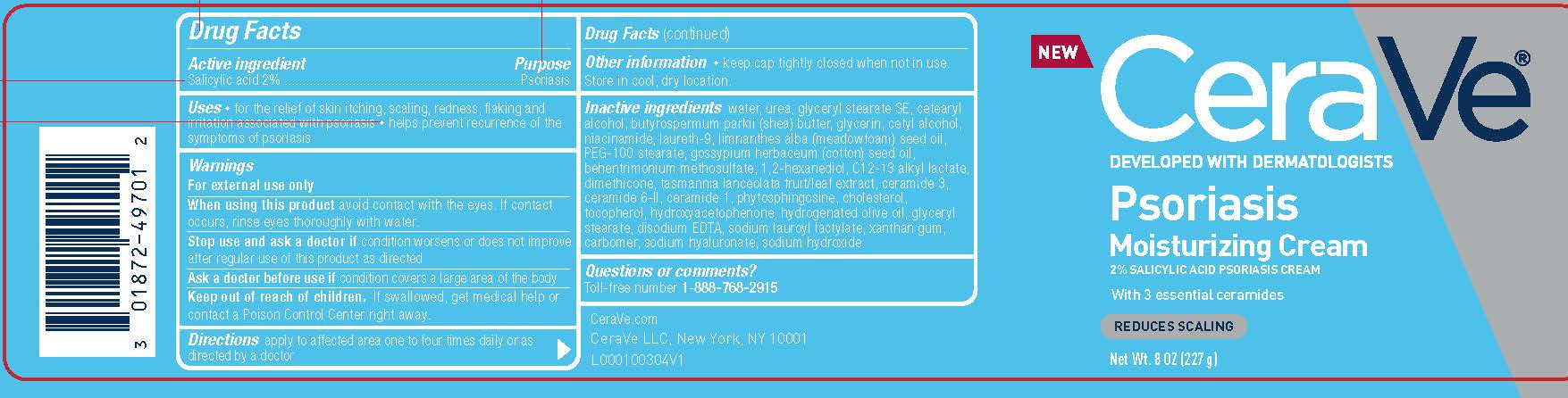 DRUG LABEL: CeraVe Developed with Dermatologists Psoriasis Moisturizing
NDC: 49967-701 | Form: CREAM
Manufacturer: L'Oreal USA Products Inc
Category: otc | Type: HUMAN OTC DRUG LABEL
Date: 20231228

ACTIVE INGREDIENTS: SALICYLIC ACID 20 mg/1 g
INACTIVE INGREDIENTS: WATER; UREA; GLYCERYL STEARATE SE; CETOSTEARYL ALCOHOL; NIACINAMIDE; POLIDOCANOL; MEADOWFOAM SEED OIL; PEG-100 STEARATE; LEVANT COTTONSEED OIL; BEHENTRIMONIUM METHOSULFATE; 1,2-HEXANEDIOL; C12-13 ALKYL LACTATE; DIMETHICONE; CERAMIDE 3; CERAMIDE 6 II; CERAMIDE 1; PHYTOSPHINGOSINE; CHOLESTEROL; TOCOPHEROL; HYDROXYACETOPHENONE; HYDROGENATED OLIVE OIL; GLYCERYL MONOSTEARATE; DISODIUM EDTA-COPPER; SODIUM LAUROYL LACTYLATE; XANTHAN GUM; CARBOMER HOMOPOLYMER TYPE B (ALLYL SUCROSE CROSSLINKED); HYALURONATE SODIUM; SODIUM HYDROXIDE

Drug Facts

Active ingredient

Salicylic acid 2%

Purpose

Psoriasis

Uses

- for the relief of skin itching, scaling, redness, flaking and irritation associated with psoriasis
- helps prevent the recurrence of the symptoms of psoriasis

Warnings

For external use only

When using this product

avoid contact with the eyes. If contact occurs, rinse eyes thoroughly with water.

Stop use and ask a doctor if

condition worsens or does not improve after regular use of this product as directed

Ask doctor before use if

condition covers a large area of the body

Keep out of reach of children.

If swallowed, get medical help or contact a Poison Control Center right away.

Directions

apply to affected area one to four times daily or as directed by a doctor

Other information

- keep cap tightly closed when not in use
- store in cool, dry location

Inactive ingredients

water, urea, glyceryl stearate SE, cetearyl alcohol, butyrospermum parkii (shea) butter, glycerin, cetyl alcohol, niacinamide, laureth-9, limnanthes alba (meadowfoam) seed oil, PEG-100 stearate, gossypium herbaceum (cotton) seed oil, behentrimonium methosulfate, 1,2-hexanediol, C12-13 alkyl lactate, dimethicone, tasmannia lanceolata fruit/leaf extract, ceramide 3, ceamide 6-II, ceramide 1, phytosphingosine, cholesterol, tocopherol, hydroxyacetophenone, hydrogenated olive oil, glyceryl stearate, disodium EDTA, sodium lauroyl lactylate, xanthan gum, carbomer, sodium hyaluronate, sodium hydroxide

Questions or comments?

Toll-free number 1-888-768-2915